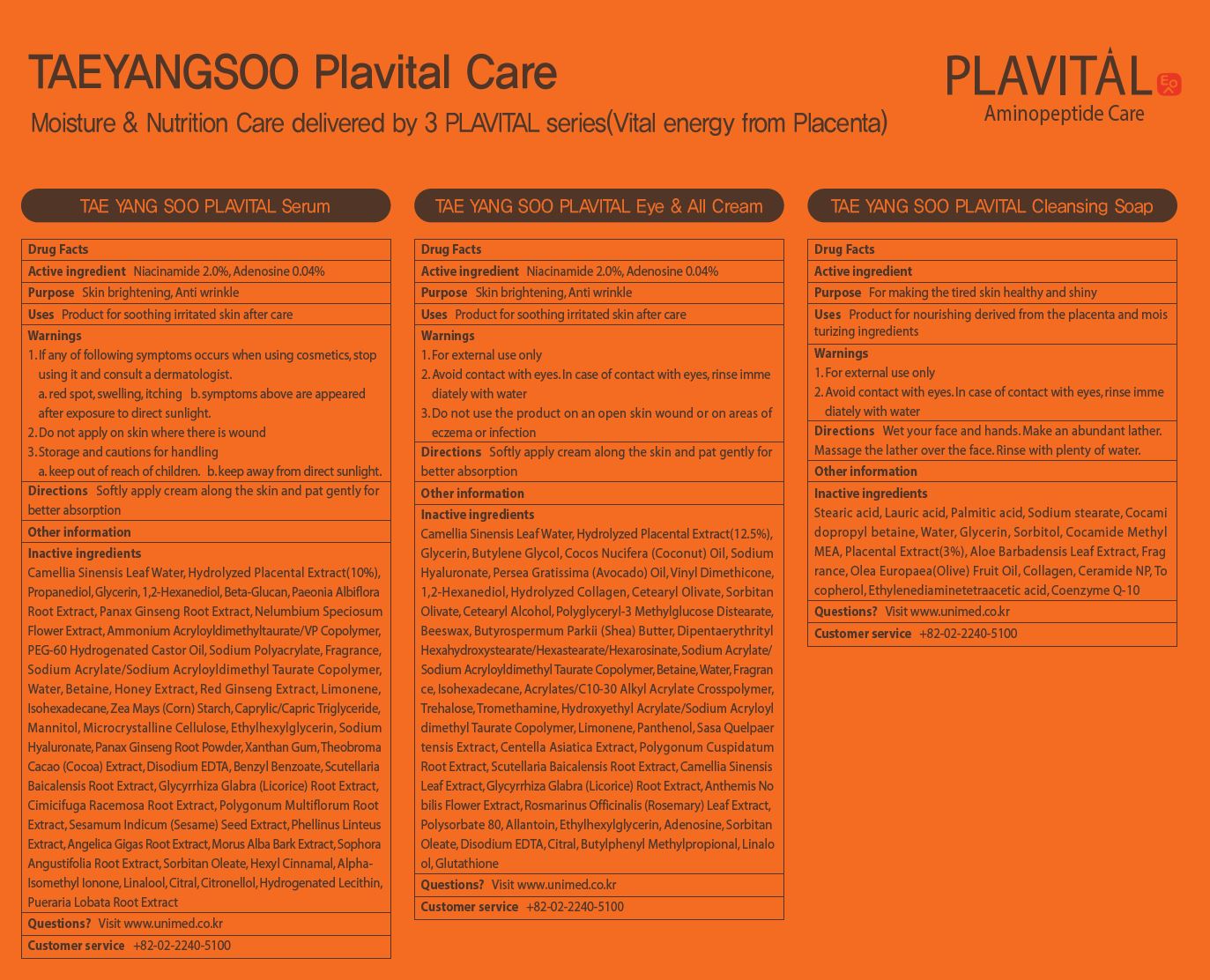 DRUG LABEL: TAEYANGSOO PLAVITAL SERUM
NDC: 73669-006 | Form: LIQUID
Manufacturer: Unimed Pharmaceuticals, Inc.
Category: otc | Type: HUMAN OTC DRUG LABEL
Date: 20210403

ACTIVE INGREDIENTS: NIACINAMIDE 2 g/100 mL; ADENOSINE 0.04 g/100 mL
INACTIVE INGREDIENTS: WATER

Drug Facts

ACTIVE INGREDIENT

adenosine, niacinamide

INACTIVE INGREDIENT

Camellia Sinensis Leaf Water, Hydrolyzed Placental Extract(10%),
Propanediol, Glycerin, 1,2-Hexanediol, Beta-Glucan, Paeonia Albiflora
Root Extract, Panax Ginseng Root Extract, Nelumbium Speciosum
Flower Extract, Ammonium Acryloyldimethyltaurate/VP Copolymer,
PEG-60 Hydrogenated Castor Oil, Sodium Polyacrylate, Fragrance,
Sodium Acrylate/Sodium Acryloyldimethyl Taurate Copolymer,
Water, Betaine, Honey Extract, Red Ginseng Extract, Limonene,
Isohexadecane, Zea Mays (Corn) Starch, Caprylic/Capric Triglyceride,
Mannitol, Microcrystalline Cellulose, Ethylhexylglycerin, Sodium
Hyaluronate, Panax Ginseng Root Powder, Xanthan Gum, Theobroma
Cacao (Cocoa) Extract, Disodium EDTA, Benzyl Benzoate, Scutellaria
Baicalensis Root Extract, Glycyrrhiza Glabra (Licorice) Root Extract,
Cimicifuga Racemosa Root Extract, Polygonum Multiflorum Root
Extract, Sesamum Indicum (Sesame) Seed Extract, Phellinus Linteus
Extract, Angelica Gigas Root Extract, Morus Alba Bark Extract, Sophora
Angustifolia Root Extract, Sorbitan Oleate, Hexyl Cinnamal, Alpha-
Isomethyl Ionone, Linalool, Citral, Citronellol, Hydrogenated Lecithin,
Pueraria Lobata Root Extract

PURPOSE

Skin brightening, Anti wrinkle

keep out of reach of the children

INDICATIONS AND USAGE

Softly apply cream along the skin and pat gently for better absorption

WARNINGS

1. If any of following symptoms occurs when using cosmetics, stop
using it and consult a dermatologist.
a. red spot, swelling, itching b. symptoms above are appeared
after exposure to direct sunlight.
2. Do not apply on skin where there is wound
3. Storage and cautions for handling
a. keep out of reach of children. b. keep away from direct sunlight.

DOSAGE AND ADMINISTRATION

external use only